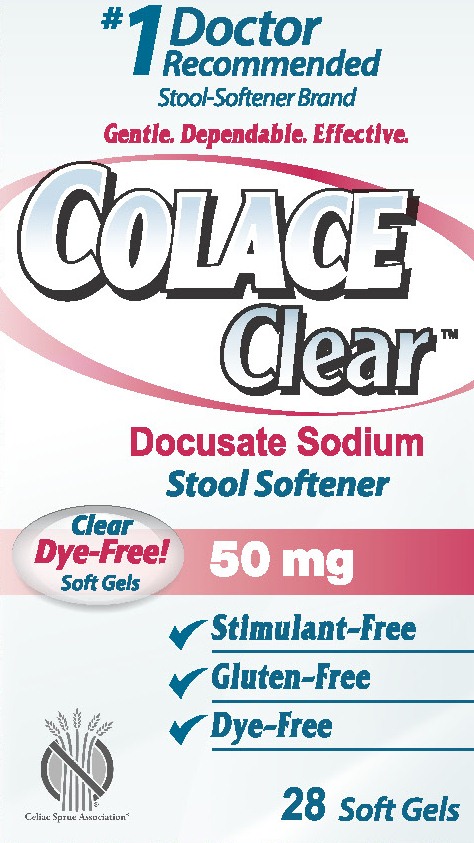 DRUG LABEL: Colace Clear
NDC: 67618-109 | Form: CAPSULE, LIQUID FILLED
Manufacturer: Purdue Products LP
Category: otc | Type: HUMAN OTC DRUG LABEL
Date: 20150128

ACTIVE INGREDIENTS: DOCUSATE SODIUM 50 mg/1 1
INACTIVE INGREDIENTS: GELATIN; GLYCERIN; POLYETHYLENE GLYCOL 400; PROPYLENE GLYCOL; SORBITOL

Drug Facts

Colace Clear 50 mg

Active ingredient
(in each soft gel)

Docusate sodium 50 mg

Purpose

Stool softener

Uses

- relieves occasional constipation (irregularity)
- generally produces bowel movement in 12 to 72 hours

Do not use

- if you are presently taking mineral oil, unless told to do so by a doctor

Ask a doctor before use if you have

- stomach pain
- nausea
- vomiting
- noticed a sudden change in bowel habits that lasts over 2 weeks

Stop use and ask a doctor if

- you have rectal bleeding or fail to have a bowel movement after use of a laxative. These could be signs of a serious condition.
- you need to use a stool softener laxative for more than 1 week

PREGNANCY OR BREAST FEEDING

If pregnant or breast-feeding, ask a health professional before use.

Keep out of reach of children. In case of overdose, get medical help or contact a Poison Control Center right away.

DOSAGE AND ADMINISTRATION

Directions: _ Take only by mouth. Doses may be taken as a single daily dose or in divided doses.

adults and children 12 years and over | take 1-6 soft gels daily
children 2 to under 12 years of age | take 1-3 soft gels daily
children under 2 years | ask a doctor

Other information

- each soft gel contains: sodium 3 mg VERY LOW SODIUM
- store at 25°C (77°F); excursions permitted between 15°-30°C (59°-86°F).
  Keep tightly closed.

Inactive ingredients

gelatin,glycerin, PEG 400, propylene glycol, sorbitol

Soft gels are imprinted with edible dye-free ink.

©2014, Purdue Products L.P.
Dist. by: Purdue Products L.P.
Stamford, CT 06901-3431
Made in the USA
303458-0A

PACKAGE LABEL

Colace Clear™ 50 mg Carton
NDC: 67818-100-28